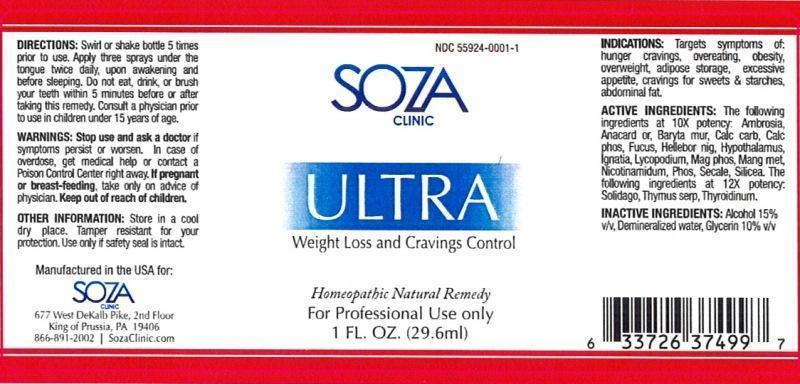 DRUG LABEL: Ultra
NDC: 55924-0001 | Form: LIQUID
Manufacturer: Soza Clinic
Category: homeopathic | Type: HUMAN PRESCRIPTION DRUG LABEL
Date: 20130529

ACTIVE INGREDIENTS: AMBROSIA ARTEMISIIFOLIA 10 [hp_X]/29.6 mL; SEMECARPUS ANACARDIUM JUICE 10 [hp_X]/29.6 mL; BARIUM CHLORIDE DIHYDRATE 10 [hp_X]/29.6 mL; OYSTER SHELL CALCIUM CARBONATE, CRUDE 10 [hp_X]/29.6 mL; TRIBASIC CALCIUM PHOSPHATE 10 [hp_X]/29.6 mL; FUCUS VESICULOSUS 10 [hp_X]/29.6 mL; HELLEBORUS NIGER ROOT 10 [hp_X]/29.6 mL; BOS TAURUS HYPOTHALAMUS 10 [hp_X]/29.6 mL; STRYCHNOS IGNATII SEED 10 [hp_X]/29.6 mL; LYCOPODIUM CLAVATUM SPORE 10 [hp_X]/29.6 mL; MAGNESIUM PHOSPHATE, DIBASIC TRIHYDRATE 10 [hp_X]/29.6 mL; MANGANESE 10 [hp_X]/29.6 mL; NIACINAMIDE 10 [hp_X]/29.6 mL; PHOSPHORUS 10 [hp_X]/29.6 mL; CLAVICEPS PURPUREA SCLEROTIUM 10 [hp_X]/29.6 mL; SILICON DIOXIDE 10 [hp_X]/29.6 mL; SOLIDAGO VIRGAUREA FLOWERING TOP 12 [hp_X]/29.6 mL; THYMUS SERPYLLUM 12 [hp_X]/29.6 mL; THYROID, UNSPECIFIED 12 [hp_X]/29.6 mL
INACTIVE INGREDIENTS: ALCOHOL; WATER; GLYCERIN

ULTRA

DOSAGE AND ADMINISTRATION

Directions: Swirl or shake bottle 5 times prior to use. Apply three sprays under the tongue twice daily, upon awakening and before sleeping. Do not eat, drink, or brush your teeth within 5 minutes before or after taking this remedy. Consult a physician prior to use in children under 15 years of age.

WARNINGS AND PRECAUTIONS

Warnings: Stop use and ask a doctor if symptoms persist or worsen. In case of overdose, get medical help or contact a Poison Control Center right away. If pregnant or breast-feeding, take only on advice of physician. Keep out of reach of children.

Other Information: Store in a cool dry place. Tamper resistant for you protection. Use only if safety seal is intact.

Keep out of reach of children.

INDICATIONS AND USAGE

Indications: Targets symptoms of: hunger cravings, overeating, obesity, overweight, adipose storage, excessive appetite, cravings for sweets and starches, abdominal fat.

ACTIVE INGREDIENT

Active Ingredients: The following ingredients at 10X potency: Ambrosia artemisiaefolia, Anacardium orientale, Baryta muriatica, Calcarea carbonica, Calcarea phosphorica, Fucus Vesiculosus, Helleborus niger, Hypothalamus, Ignatia amara, Lycopodium clavatum, Magnesia phosphorica, Manganum metallicum, Nicotinamidum, Phosphorus, Secale Cornutum, Silicea, The following ingredients at 12X potency Solidago virgaurea, Thymus serpyllum, Thyroidinum.

INACTIVE INGREDIENT

Inactive Ingredients: Alcohol 15% v/v, Demineralized water, Glycerin 10% v/v

PURPOSE

Indications: Targets symptoms of:

- hunger cravings
- overeating
- obesity
- overweight
- adipose storage
- excessive appetite
- cravings for sweets and starches
- abdominal fat